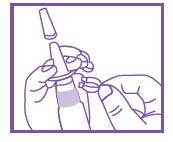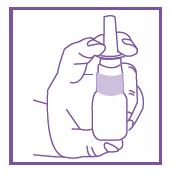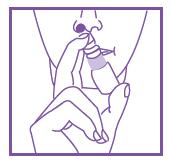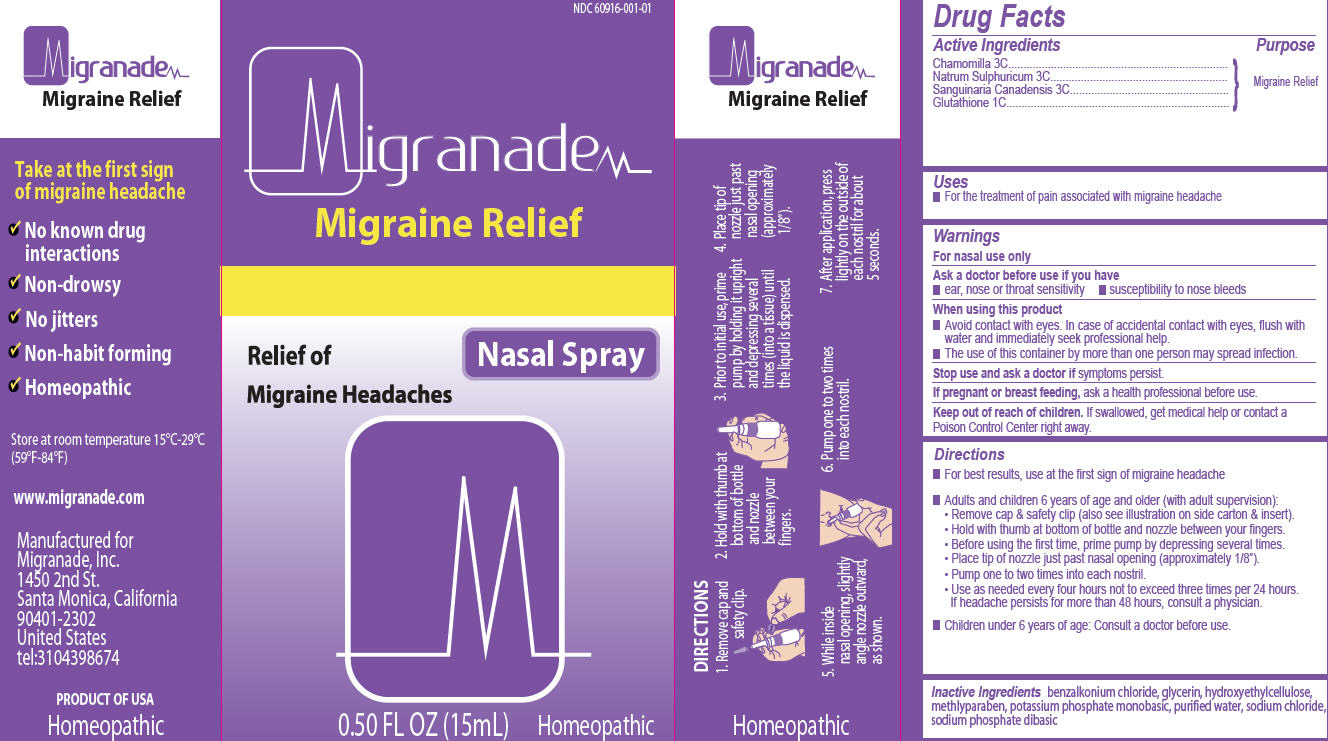 DRUG LABEL: Migranade
NDC: 60916-001 | Form: SPRAY
Manufacturer: Migranade Inc.
Category: homeopathic | Type: HUMAN OTC DRUG LABEL
Date: 20140122

ACTIVE INGREDIENTS: CHAMOMILE 3 [hp_C]/15 mL; SODIUM SULFATE 3 [hp_C]/15 mL; SANGUINARIA CANADENSIS ROOT 3 [hp_C]/15 mL; GLUTATHIONE 1 [hp_C]/15 mL
INACTIVE INGREDIENTS: BENZALKONIUM CHLORIDE; GLYCERIN; HYDROXYETHYL CELLULOSE (100 MPA.S AT 2%); METHYLPARABEN; POTASSIUM PHOSPHATE, MONOBASIC; WATER; SODIUM CHLORIDE; SODIUM PHOSPHATE, DIBASIC, ANHYDROUS

Migranade Migraine Relief Nasal Spray

Active Ingredients

Chamomilla 3C

Natrum Sulphuricum 3C

Sanguinaria Canadensis 3C

Glutathione 1C

Purpose

Migraine Relief

Uses

For the treatment of pain associated with migraine headache.

Warnings

For nasal use only

Ask a doctor before use if you have

- ear, nose or throat sensitivity
- susceptibility to nose bleeds

When using this product

- Avoid contact with eyes. In case of accidental contact with eyes, flush with water and immediately seek professional help.
- The use of this container by more than one person may spread infection.

Stop use and ask a doctor

if symptoms persist.

If pregnant or breast feeding,

ask a health professional before use.

Keep out of reach of children.

If swallowed, get medical help or contact a Poison Control Center right away.

Directions

- For best results, use at the first sign of migraine headache
- Adults and children 6 years of age and older (with adult supervision):
  - Remove cap & safety clip (also see illustration on side carton & insert).
  - Hold with thumb at bottom of bottle and nozzle between your fingers.
  - Before using the first time, prime pump by depressing several times.
  - Place tip o nozzle just past nasal opening (approximately 1/8”).
  - Pump one to two times into each nostril.
  - Use as needed every four hours not exceed three times per 24 hours. If headache persists for more than 48 hours, consult a physician.
- Children under 6 years of age: Consult a doctor before use.

Inactive Ingredients

benzalkonium chloride, glycerin, hydroxyethylcellulose, methylparaben, potassium phosphate monobasic, purified water, sodium chloride, sodium phosphate dibasic

Take at the first sign of migraine headache

 No known drug interactions
 Non-drowsy
 No jitters
 Non-habit forming
 Homeopathic

Store at room temperature 15°C-29C-29°C (59°F-84°F)
www.migranade.com
Manufactured for Migranade, Inc.
1450 2nd St.
Santa Monica, California 90401-2302
United States
tel: 3104398674

Product of USA Homeopathic

Patient Information

Migranade Migraine Relief
Non-Drowsy

Relief of Migraine Headache

Homeopathic

DIRECTIONS: Adults and children 6 years of age and older (with adult supervision):

1. Remove cap and safety clip.

2. Hold with thumb at bottom of bottle and nozzle between your fingers.

3. Before using the first time, prime pump by depressing several times.

4. Place tip of nozzle just past nasal opening (approximately 1/8”).

5. Pump one to two times into each nostril.

6. Use as needed every four hours not to exceed three times per 24 hours. if headache persists for more than 48 hours, consult a physician.

Children under 6 years of age: Consult a doctor before use.

Active Ingredients:
Chamomilla 3C,
Natrum Sulphuricum 3C,
Sanguinaria Canadensis 3C,
Glutathione 1C

Inactive Ingredients:
benzalkonium chloride, glycerin, hydroxyethylcellulose, methlyparaben, potassium phosphate monobasic, purified water, sodium chloride, sodium phosphate dibasic

Warnings:
For nasal use only
Ask a doctor before use if you have

 ear, nose or throat sensitivity
 susceptibility to nose bleeds

When using this product

 Avoid contact with eyes. In case of accidental contact with eyes, flush with water and immediately seek professional help.
 The use of this container by more than one person may spread infection.

Stop use and ask a doctor if symptoms persist.

If pregnant or breast feeding, ask a health professional before use.

Keep out of reach of children. If swallowed, get medical help or contact a Poison Control Center right away.

Take at the first sign of migraine headache.

Migranade Migraine Relief

- No known drug interactions
- Non-drowsy
- No jitters
- Non-habit forming
- Homeopathic

Product is naturally dark in color.

www.migranade.com

Manufactured for:
Migranade Inc.
Santa Monica, California
90401-2302
United States
tel:3104398674

PRODUCT OF USA
Homeopathic

Package/Label Principal Display Panel

Carton Label